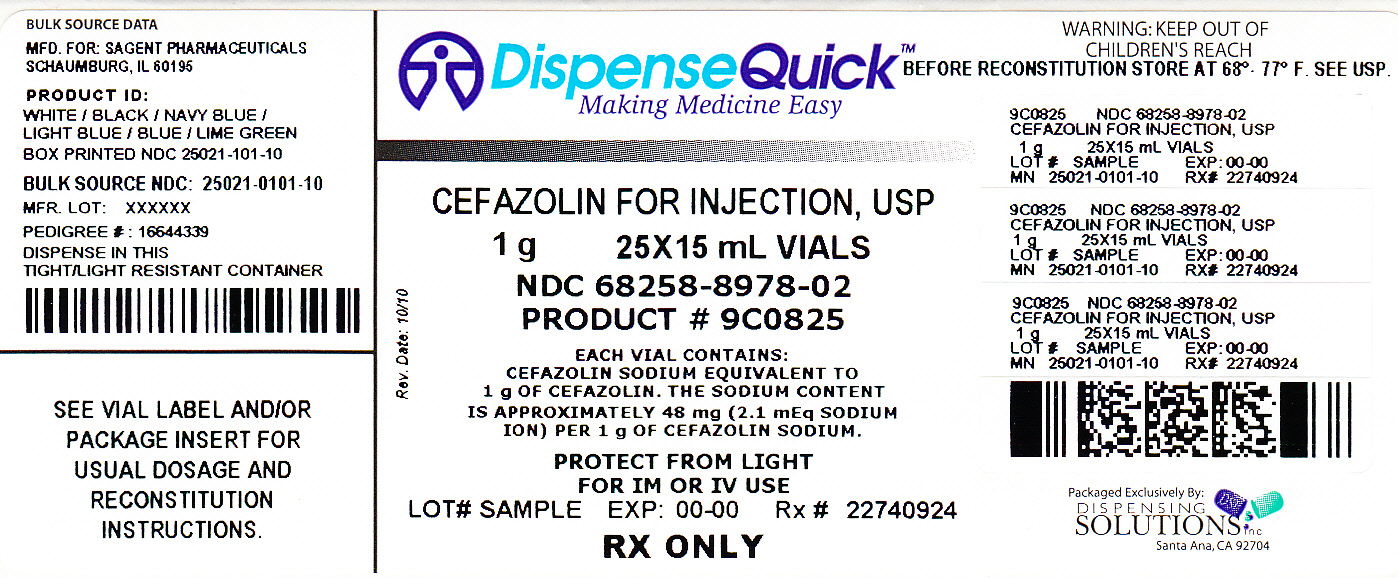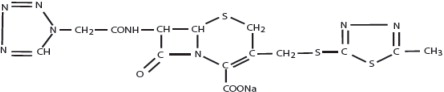 DRUG LABEL: Cefazolin
NDC: 68258-8978 | Form: INJECTION, POWDER, FOR SOLUTION
Manufacturer: Dispensing Solutions, Inc.
Category: prescription | Type: HUMAN PRESCRIPTION DRUG LABEL
Date: 20111003

ACTIVE INGREDIENTS: cefazolin sodium 1 g/3 mL

Cefazolin for Injection, USP
For IM or IV Use

SAGENT™

Rx Only

To reduce the development of drug-resistant bacteria and maintain the effectiveness of Cefazolin for Injection, USP and other antibacterial drugs, Cefazolin for Injection, USP should be used only to treat or prevent infections that are proven or strongly suspected to be caused by bacteria.

DESCRIPTION

Cefazolin for Injection, USP is a semi-synthetic cephalosporin for parenteral administration. It is the sodium salt of 3-{[(5-methyl-1,3,4-thiadiazol-2-yl)thio]-methyl}-8-oxo-7-[2-(1H-tetrazol-1-yl) acetamido]-5-thia-1-azabicyclo[4.2.0]oct-2-ene-2-carboxylic acid.

Structural Formula:

Each vial contains 48 mg of sodium/1 gram of cefazolin sodium.

Each vial contains cefazolin sodium equivalent to 500 mg or 1 gram cefazolin.

CLINICAL PHARMACOLOGY

After intramuscular administration of cefazolin to normal volunteers, the mean serum concentrations were 37 mcg/mL at 1 hour and 3 mcg/mL at 8 hours following a 500 mg dose, and 64 mcg/mL at 1 hour and 7 mcg/mL at 8 hours following a 1 gram dose.

Studies have shown that following intravenous administration of cefazolin to normal volunteers, mean serum concentrations peaked at approximately 185 mcg/mL and were approximately 4 mcg/mL at 8 hours for a 1 gram dose.

The serum half-life for cefazolin is approximately 1.8 hours following IV administration and approximately 2 hours following IM administration.

In a study (using normal volunteers) of constant intravenous infusion with dosages of 3.5 mg/kg for 1 hour (approximately 250 mg) and 1.5 mg/kg the next 2 hours (approximately 100 mg), cefazolin produced a steady serum level at the third hour of approximately 28 mcg/mL.

Studies in patients hospitalized with infections indicate that cefazolin produces mean peak serum levels approximately equivalent to those seen in normal volunteers.

Bile levels in patients without obstructive biliary disease can reach or exceed serum levels by up to 5 times; however, in patients with obstructive biliary disease, bile levels of cefazolin are considerably lower than serum levels (< 1 mcg/mL).

In synovial fluid, the level of cefazolin becomes comparable to that reached in serum at about 4 hours after drug administration.

Studies of cord blood show prompt transfer of cefazolin across the placenta. Cefazolin is present in very low concentrations in the milk of nursing mothers.

Cefazolin is excreted unchanged in the urine. In the first 6 hours approximately 60% of the drug is excreted in the urine and this increases to 70% to 80% within 24 hours. Cefazolin achieves peak urine concentrations of approximately 2,400 mcg/mL and 4,000 mcg/mL respectively following 500 mg and 1 gram intramuscular doses.

In patients undergoing peritoneal dialysis (2 L/hr.), cefazolin produced mean serum levels of approximately 10 and 30 mcg/mL after 24 hours' instillation of a dialyzing solution containing 50 mg/L and 150 mg/L, respectively. Mean peak levels were 29 mcg/mL (range 13 to 44 mcg/mL) with 50 mg/L (3 patients), and 72 mcg/mL (range 26 to 142 mcg/mL) with 150 mg/L (6 patients). Intraperitoneal administration of cefazolin is usually well tolerated.

Controlled studies on adult normal volunteers, receiving 1 gram 4 times a day for 10 days, monitoring CBC, SGOT, SGPT, bilirubin, alkaline phosphatase, BUN, creatinine, and urinalysis, indicated no clinically significant changes attributed to cefazolin.

Microbiology

In vitro tests demonstrate that the bactericidal action of cephalosporins results from inhibition of cell wall synthesis. Cefazolin has been shown to be active against most strains of the following microorganisms, both in vitro and in clinical infections as described in INDICATIONS AND USAGE.

Gram-Positive Aerobes

Staphylococcus aureus (including beta-lactamase-producing strains)
Staphylococcus epidermidis
Streptococcus pyogenes, Streptococcus agalactiae, and other strains of streptococci
Streptococcus pneumoniae

Methicillin-resistant staphylococci are uniformly resistant to cefazolin, and many strains of enterococci are resistant.

Gram-Negative Aerobes

Escherichia coli
Proteus mirabilis

Most strains of indole positive Proteus (Proteus vulgaris), Enterobacter spp., Morganella morganii, Providencia rettgeri, Serratia spp., and Pseudomonas spp. are resistant to cefazolin.

Susceptibility Testing

Diffusion Techniques

Quantitative methods that require measurement of zone diameters provide reproducible estimates of the susceptibility of bacteria to antimicrobial compounds. One such standardized procedure^1 that has been recommended for use with disks to test the susceptibility of microorganisms to cefazolin uses the 30 mcg cefazolin disk. Results of the standardized single-disk susceptibility test^1 with a 30 mcg cefazolin disk should be interpreted according to the following criteria:

RECOMMENDED RANGES FOR CEFAZOLIN SUSCEPTIBILITY TESTING
Zone Diameter (mm) | Interpretation
≥ 18 | Susceptible (S)
15 to 17 | Intermediate (I)
≤ 14 | Resistant (R)

Standardized single-disk susceptibility test should be performed ONLY with a 30 mcg cefazolin disk.

A report of “Susceptible” indicates that the pathogen is likely to be inhibited by usually achievable concentrations of the antimicrobial compound in the blood. A report of “Intermediate” indicates that the result should be considered equivocal, and, if the microorganism is not fully susceptible to alternative, clinically feasible drugs, the test should be repeated. This category implies possible clinical applicability in body sites where the drug is physiologically concentrated or in situations where high dosage of drug can be used. This category also provides a buffer zone that prevents small uncontrolled technical factors from causing major discrepancies in interpretation. A report of “Resistant” indicates that usually achievable concentrations of the antimicrobial compound in the blood are unlikely to be inhibitory and that other therapy should be selected.

Standardized susceptibility test procedures require the use of laboratory control microorganisms. The 30 mcg cefazolin disk should provide the following zone diameters in these laboratory test quality control strains:

Microorganism | Zone Diameter (mm)
E. coli ATCC 25922 | 21 to 27
S. aureus ATCC 25923 | 29 to 35

The cefazolin disk should not be used for testing susceptibility to other cephalosporins.

Dilution Techniques

Quantitative methods that are used to determine minimum inhibitory concentrations provide reproducible estimates of the susceptibility of bacteria to antimicrobial compounds. One such standardized procedure uses a standardized dilution method^2 (broth, agar, or microdilution) or equivalent with cefazolin powder. The MIC values obtained should be interpreted according to the following criteria:

MIC (mcg/mL) | Interpretation
≤ 16 | Susceptible (S)
≥ 64 | Resistant (R)

Interpretation should be as stated above for results using diffusion techniques.

As with standard diffusion techniques, dilution methods require the use of laboratory control microorganisms. Standard cefazolin powder should provide the following MIC values:

Microorganism | MIC (mcg/mL)
S. aureus ATCC 25923 | 0.25 to 1
E. coli ATCC 25922 | 1 to 4

INDICATIONS AND USAGE

Cefazolin for Injection, USP is indicated in the treatment of the following serious infections due to susceptible organisms:

Respiratory Tract Infections: Due to S. pneumoniae, S. aureus (including beta-lactamase-producing strains) and S. pyogenes.

Injectable benzathine penicillin is considered to be the drug of choice in treatment and prevention of streptococcal infections, including the prophylaxis of rheumatic fever.

Cefazolin for Injection, USP is effective in the eradication of streptococci from the nasopharynx; however, data establishing the efficacy of cefazolin in the subsequent prevention of rheumatic fever are not available.

Urinary Tract Infections: Due to E. coli, P. mirabilis.

Skin and Skin Structure Infections: Due to S. aureus (including beta-lactamase-producing strains), S. pyogenes, and other strains of streptococci.

Biliary Tract Infections: Due to E. coli, various strains of streptococci, P. mirabilis, and S. aureus.

Bone and Joint Infections: Due to S. aureus.

Genital Infections: (i.e., prostatitis, epididymitis) due to E. coli, P. mirabilis.

Septicemia: Due to S. pneumoniae, S. aureus (including beta-lactamase-producing strains), P. mirabilis, E. coli.

Endocarditis: Due to S. aureus (including beta-lactamase-producing strains) and S. pyogenes.

Appropriate culture and susceptibility studies should be performed to determine susceptibility of the causative organism to cefazolin.

Perioperative Prophylaxis: The prophylactic administration of Cefazolin for Injection, USP preoperatively, intraoperatively, and postoperatively may reduce the incidence of certain postoperative infections in patients undergoing surgical procedures which are classified as contaminated or potentially contaminated (e.g., vaginal hysterectomy and cholecystectomy in high-risk patients such as those older than 70 years, with acute cholecystitis, obstructive jaundice, or common duct bile stones).

The perioperative use of Cefazolin for Injection, USP also may be effective in surgical patients in whom infection at the operative site would present a serious risk (e.g., during open-heart surgery and prosthetic arthroplasty).

The prophylactic administration of Cefazolin for Injection, USP should usually be discontinued within a 24-hour period after the surgical procedure. In surgery where the occurrence of infection may be particularly devastating (e.g., open-heart surgery and prosthetic arthroplasty), the prophylactic administration of Cefazolin for Injection, USP may be continued for 3 to 5 days following the completion of surgery.

If there are signs of infection, specimens for cultures should be obtained for the identification of the causative organism so that appropriate therapy may be instituted.

(See DOSAGE AND ADMINISTRATION.)

To reduce the development of drug-resistant bacteria and maintain the effectiveness of Cefazolin for Injection, USP and other antibacterial drugs, Cefazolin for Injection, USP should be used only to treat or prevent infections that are proven or strongly suspected to be caused by susceptible bacteria. When culture and susceptibility information are available, they should be considered in selecting or modifying antibacterial therapy. In the absence of such data, local epidemiology and susceptibility patterns may contribute to the empiric selection of therapy.

CONTRAINDICATIONS

CEFAZOLIN IS CONTRAINDICATED IN PATIENTS WITH KNOWN ALLERGY TO THE CEPHALOSPORIN GROUP OF ANTIBIOTICS.

WARNINGS

BEFORE THERAPY WITH CEFAZOLIN IS INSTITUTED, CAREFUL INQUIRY SHOULD BE MADE TO DETERMINE WHETHER THE PATIENT HAS HAD PREVIOUS HYPERSENSITIVITY REACTIONS TO CEFAZOLIN, CEPHALOSPORINS, PENICILLINS, OR OTHER DRUGS. IF THIS PRODUCT IS GIVEN TO PENICILLIN-SENSITIVE PATIENTS, CAUTION SHOULD BE EXERCISED BECAUSE CROSS-HYPERSENSITIVITY AMONG BETA-LACTAM ANTIBIOTICS HAS BEEN CLEARLY DOCUMENTED AND MAY OCCUR IN UP TO 10% OF PATIENTS WITH A HISTORY OF PENICILLIN ALLERGY. IF AN ALLERGIC REACTION TO CEFAZOLIN OCCURS, DISCONTINUE TREATMENT WITH THE DRUG. SERIOUS ACUTE HYPERSENSITIVITY REACTIONS MAY REQUIRE TREATMENT WITH EPINEPHRINE AND OTHER EMERGENCY MEASURES, INCLUDING OXYGEN, IV FLUIDS, IV ANTIHISTAMINES, CORTICOSTEROIDS, PRESSOR AMINES, AND AIRWAY MANAGEMENT, AS CLINICALLY INDICATED.

Clostridium difficile associated diarrhea (CDAD) has been reported with use of nearly all antibacterial agents, including cefazolin, and may range in severity from mild diarrhea to fatal colitis. Treatment with antibacterial agents alters the normal flora of the colon leading to overgrowth of C. difficile.

C. difficile produces toxins A and B which contribute to the development of CDAD. Hypertoxin producing strains of C. difficile cause increased morbidity and mortality, as these infections can be refractory to antimicrobial therapy and may require colectomy. CDAD must be considered in all patients who present with diarrhea following antibiotic use. Careful medical history is necessary since CDAD has been reported to occur over two months after the administration of antibacterial agents.

If CDAD is suspected or confirmed, ongoing antibiotic use not directed against C. difficile may need to be discontinued. Appropriate fluid and electrolyte management, protein supplementation, antibiotic treatment of C. difficile, and surgical evaluation should be instituted as clinically indicated.

PRECAUTIONS

General

Prolonged use of cefazolin may result in the overgrowth of nonsusceptible organisms. Careful clinical observation of the patient is essential.

When cefazolin is administered to patients with low urinary output because of impaired renal function, lower daily dosage is required (See DOSAGE AND ADMINISTRATION).

As with other β-lactam antibiotics, seizures may occur if inappropriately high doses are administered to patients with impaired renal function (see DOSAGE AND ADMINISTRATION).

Cefazolin, as with all cephalosporins, should be prescribed with caution in individuals with a history of gastrointestinal disease, particularly colitis.

Cephalosporins may be associated with a fall in prothrombin activity. Those at risk include patients with renal or hepatic impairment or poor nutritional state, as well as patients receiving a protracted course of antimicrobial therapy, and patients previously stabilized on anticoagulant therapy. Prothrombin time should be monitored in patients at risk and exogenous vitamin K administered as indicated.

Prescribing cefazolin in the absence of a proven or strongly suspected bacterial infection or a prophylactic indication is unlikely to provide benefit to the patient and increases the risk of the development of drug-resistant bacteria.

Drug Interactions

Probenecid may decrease renal tubular secretion of cephalosporins when used concurrently, resulting in increased and more prolonged cephalosporin blood levels.

Drug/Laboratory Test Interactions

A false positive reaction for glucose in the urine may occur with Benedict's solution, Fehling's solution or with CLINITEST® tablets, but not with enzyme-based tests, such as CLINISTIX®.

Positive direct and indirect antiglobulin (Coombs') tests have occurred; these may also occur in neonates whose mothers received cephalosporins before delivery.

Information for Patients

Diarrhea is a common problem caused by antibiotics which usually ends when the antibiotic is discontinued. Sometimes after starting treatment with antibiotics, patients can develop watery and bloody stools (with or without stomach cramps and fever) even as late as two or more months after having taken the last dose of the antibiotic. If this occurs, patients should contact their physician as soon as possible.

Patients should be counseled that antibacterial drugs including cefazolin, should only be used to treat bacterial infections. They do not treat viral infections (e.g., the common cold). When cefazolin is prescribed to treat a bacterial infection, patients should be told that although it is common to feel better early in the course of therapy, the medication should be taken exactly as directed. Skipping doses or not completing the full course of therapy may: (1) decrease the effectiveness of the immediate treatment, and (2) increase the likelihood that bacteria will develop resistance and will not be treatable by cefazolin or other antibacterial drugs in the future.

Carcinogenesis/Mutagenesis

Mutagenicity studies and long-term studies in animals to determine the carcinogenic potential of cefazolin have not been performed.

Pregnancy

TERATOGENIC EFFECTS

Teratogenic Effects: Pregnancy Category B. Reproduction studies have been performed in rats, mice, and rabbits at doses up to 25 times the human dose and have revealed no evidence of impaired fertility or harm to the fetus due to cefazolin. There are, however, no adequate and well-controlled studies in pregnant women. Because animal reproduction studies are not always predictive of human response, this drug should be used during pregnancy only if clearly needed.

Labor and Delivery

When cefazolin has been administered prior to caesarean section, drug levels in cord blood have been approximately one quarter to one third of maternal drug levels. The drug appears to have no adverse effect on the fetus.

Nursing Mothers

Cefazolin is present in very low concentrations in the milk of nursing mothers. Caution should be exercised when cefazolin is administered to a nursing woman.

Pediatric Use

Safety and effectiveness for use in premature infants and neonates have not been established. See DOSAGE AND ADMINISTRATION for recommended dosage in pediatric patients older than 1 month.

Geriatric Use

Of the 920 subjects who received cefazolin in clinical studies, 313 (34%) were 65 years and over, while 138 (15%) were 75 years and over. No overall differences in safety or effectiveness were observed between these subjects and younger subjects. Other reported clinical experience has not identified differences in responses between the elderly and younger patients, but greater sensitivity of some older individuals cannot be ruled out.

This drug is known to be substantially excreted by the kidney, and the risk of toxic reactions to this drug may be greater in patients with impaired renal function. Because elderly patients are more likely to have decreased renal function, care should be taken in dose selection, and it may be useful to monitor renal function (see PRECAUTIONS, General and DOSAGE AND ADMINISTRATION).

ADVERSE REACTIONS

The following reactions have been reported:

Gastrointestinal

Diarrhea, oral candidiasis (oral thrush), vomiting, nausea, stomach cramps, anorexia, and pseudomembranous colitis. Onset of pseudomembranous colitis symptoms may occur during or after antibiotic treatment (see WARNINGS). Nausea and vomiting have been reported rarely.

Allergic

Anaphylaxis, eosinophilia, itching, drug fever, skin rash, Stevens-Johnson syndrome.

Hematologic

Neutropenia, leukopenia, thrombocytopenia, thrombocythemia.

Hepatic

Transient rise in SGOT, SGPT, and alkaline phosphatase levels has been observed. As with other cephalosporins, reports of hepatitis have been received.

Renal

As with other cephalosporins, reports of increased BUN and creatinine levels, as well as renal failure, have been received.

Local Reactions

Rare instances of phlebitis have been reported at site of injection. Pain at the site of injection after intramuscular administration has occurred infrequently. Some induration has occurred.

Other Reactions

Genital and anal pruritus (including vulvar pruritus, genital moniliasis, and vaginitis).

Cephalosporin-Class Adverse Reactions

In addition to the adverse reactions listed above that have been observed in patients treated with cefazolin, the following adverse reactions and altered laboratory tests have been reported for cephalosporin-class antibiotics:

Adverse Reactions

Allergic reactions, urticaria, serum-sickness-like reaction, erythema multiforme, toxic epidermal necrolysis, colitis, renal dysfunction, toxic nephropathy, abdominal pain, reversible hyperactivity, hypertonia, hepatic dysfunction including cholestasis, aplastic anemia, hemolytic anemia, hemorrhage, and superinfection.

Altered Laboratory Tests

Prolonged prothrombin time, positive direct Coombs' test, false-positive test for urinary glucose, elevated bilirubin, elevated LDH, increased creatinine, pancytopenia, and agranulocytosis.

Several cephalosporins have been implicated in triggering seizures, particularly in patients with renal impairment when the dosage was not reduced (see DOSAGE AND ADMINISTRATION). If seizures associated with drug therapy occur, the drug should be discontinued. Anticonvulsant therapy can be given if clinically indicated.

DOSAGE AND ADMINISTRATION

Usual Adult Dosage

Type of Infection | Dose | Frequency
Moderate to severe infections | 500 mg to 1 gram | every 6 to 8 hours
Mild infections caused by susceptible gram-positive cocci | 250 mg to 500 mg | every 8 hours
Acute, uncomplicated urinary tract infections | 1 gram | every 12 hours
Pneumococcal pneumonia | 500 mg | every 12 hours
Severe, life-threatening infections (e.g., endocarditis, septicemia)* | 1 gram to 1.5 grams | every 6 hours
*In rare instances, doses of up to 12 grams of cefazolin per day have been used.

Perioperative Prophylactic Use

To prevent postoperative infection in contaminated or potentially contaminated surgery, recommended doses are:

1. 1 gram IV or IM administered 1/2 hour to 1 hour prior to the start of surgery.
2. For lengthy operative procedures (e.g., 2 hours or more), 500 mg to 1 gram IV or IM during surgery (administration modified depending on the duration of the operative procedure).
3. 500 mg to 1 gram IV or IM every 6 to 8 hours for 24 hours postoperatively.

It is important that (1) the preoperative dose be given just (1/2 to 1 hour) prior to the start of surgery so that adequate antibiotic levels are present in the serum and tissues at the time of initial surgical incision; and (2) cefazolin for injection be administered, if necessary, at appropriate intervals during surgery to provide sufficient levels of the antibiotic at the anticipated moments of greatest exposure to infective organisms.

In surgery where the occurrence of infection may be particularly devastating (e.g., open-heart surgery and prosthetic arthroplasty), the prophylactic administration of cefazolin for injection may be continued for 3 to 5 days following the completion of surgery.

Dosage Adjustment for Patients With Reduced Renal Function

Cefazolin may be used in patients with reduced renal function with the following dosage adjustments: Patients with a creatinine clearance of 55 mL/min. or greater or a serum creatinine of 1.5 mg % or less can be given full doses. Patients with creatinine clearance rates of 35 to 54 mL/min. or serum creatinine of 1.6 to 3 mg % can also be given full doses but dosage should be restricted to at least 8 hour intervals. Patients with creatinine clearance rates of 11 to 34 mL/min. or serum creatinine of 3.1 to 4.5 mg % should be given 1/2 the usual dose every 12 hours. Patients with creatinine clearance rates of 10 mL/min. or less or serum creatinine of 4.6 mg % or greater should be given 1/2 the usual dose every 18 to 24 hours. All reduced dosage recommendations apply after an initial loading dose appropriate to the severity of the infection. Patients undergoing peritoneal dialysis: See CLINICAL PHARMACOLOGY.

Pediatric Dosage

In pediatric patients, a total daily dosage of 25 to 50 mg/kg (approximately 10 to 20 mg/lb) of body weight, divided into 3 or 4 equal doses, is effective for most mild to moderately severe infections. Total daily dosage may be increased to 100 mg/kg (45 mg/lb) of body weight for severe infections. Since safety for use in premature infants and in neonates has not been established, the use of cefazolin in these patients is not recommended.

Pediatric Dosage Guide
Weight |  | 25 mg/kg/day Divided into 3 Doses |  | 25 mg/kg/day Divided into 4 Doses
Lbs | Kg | Approximate Single Dose mg/q8h | Vol. (mL) needed with dilution of 125 mg/mL | Approximate Single Dose mg/q6h | Vol. (mL) needed with dilution of 125 mg/mL
10 | 4.5 | 40 mg | 0.35 mL | 30 mg | 0.25 mL
20 | 9 | 75 mg | 0.6 mL | 55 mg | 0.45 mL
30 | 13.6 | 115 mg | 0.9 mL | 85 mg | 0.7 mL
40 | 18.1 | 150 mg | 1.2 mL | 115 mg | 0.9 mL
50 | 22.7 | 190 mg | 1.5 mL | 140 mg | 1.1 mL

Weight |  | 50 mg/kg/day Divided into 3 Doses |  | 50 mg/kg/day Divided into 4 Doses
Lbs | Kg | Approximate Single Dose mg/q8h | Vol. (mL) needed with dilution of 225 mg/mL | Approximate Single Dose mg/q6h | Vol. (mL) needed with dilution of 225 mg/mL
10 | 4.5 | 75 mg | 0.35 mL | 55 mg | 0.25 mL
20 | 9 | 150 mg | 0.7 mL | 110 mg | 0.5 mL
30 | 13.6 | 225 mg | 1 mL | 170 mg | 0.75 mL
40 | 18.1 | 300 mg | 1.35 mL | 225 mg | 1 mL
50 | 22.7 | 375 mg | 1.7 mL | 285 mg | 1.25 mL

In pediatric patients with mild to moderate renal impairment (creatinine clearance of 70 to 40 mL/min.), 60 percent of the normal daily dose given in equally divided doses every 12 hours should be sufficient. In patients with moderate impairment (creatinine clearance of 40 to 20 mL/min.), 25 percent of the normal daily dose given in equally divided doses every 12 hours should be adequate. Pediatric patients with severe renal impairment (creatinine clearance of 20 to 5 mL/min.) may be given 10 percent of the normal daily dose every 24 hours. All dosage recommendations apply after an initial loading dose.

Reconstitution

Preparation of Parenteral Solution

Parenteral drug products should be SHAKEN WELL when reconstituted, and inspected visually for particulate matter prior to administration. If particulate matter is evident in reconstituted fluids, the drug solutions should be discarded.

When reconstituted or diluted according to the instructions below, Cefazolin for Injection is stable for 24 hours at room temperature or for 10 days if stored under refrigeration (5°C or 41°F).

Reconstituted solutions may range in color from pale yellow to yellow without a change in potency.

Single-Dose Vials

For IM injection, IV direct (bolus) injection or IV infusion, reconstitute with Sterile Water for Injection according to the following table. SHAKE WELL.

Vial Size | Amount of Diluent | Approximate Concentration | Approximate Available Volume
500 mg | 2 mL | 225 mg/mL | 2.2 mL
1 g | 2.5 mL | 330 mg/mL | 3 mL

Administration

Intramuscular Administration

Reconstitute vials with Sterile Water for Injection according to the dilution table above. Shake well until dissolved. Cefazolin for Injection should be injected into a large muscle mass. Pain on injection is infrequent with Cefazolin for Injection.

Intravenous Administration

Direct (bolus) injection: Following reconstitution according to the above table, further dilute vials with approximately 5 mL Sterile Water for Injection. Inject the solution slowly over 3 to 5 minutes, directly or through tubing for patients receiving parenteral fluids (see list below).

Intermittent or continuous infusion: Dilute reconstituted Cefazolin for Injection in 50 to 100 mL of 1 of the following solutions:

Sodium Chloride Injection, USP
5% or 10% Dextrose Injection, USP
5% Dextrose in Lactated Ringer's Injection, USP
5% Dextrose and 0.9% Sodium Chloride Injection, USP
5% Dextrose and 0.45% Sodium Chloride Injection, USP
5% Dextrose and 0.2% Sodium Chloride Injection, USP
Lactated Ringer's Injection, USP
Invert Sugar 5% or 10% in Sterile Water for Injection
Ringer's Injection, USP
5% Sodium Bicarbonate Injection, USP

HOW SUPPLIED

Cefazolin for Injection, USP, equivalent to 500 mg or 1 g cefazolin per vial, is supplied as follows:

NDC | Cefazolin for Injection, USP | Package Factor
25021-100-10 | 500 mg Single-Dose Vial | 25 vials per carton
25021-101-10 | 1 gram Single-Dose Vial | 25 vials per carton

As with other cephalosporins, Cefazolin for Injection, USP tends to darken depending on storage conditions; within the stated recommendations, however, product potency is not adversely affected.

Storage Conditions

Before reconstitution store at 20º to 25ºC (68º to 77ºF). [See USP Controlled Room Temperature.]

Protect from light.

Sterile, Nonpyrogenic, Preservative-free.

The container closure is not made with natural rubber latex.

REFERENCES

1. National Committee for Clinical Laboratory Standards (NCCLS). January 2003. Performance Standards for Antimicrobial Disk Susceptibility Tests; Approved Standard-Eighth Edition. NCCLS Document M2-A8 and Disk Diffusion Supplemental Tables M100-S13. NCCLS, Wayne, PA, USA.
2. National Committee for Clinical Laboratory Standards (NCCLS). January 2003. Methods for Dilution Antimicrobial Susceptibility Tests for Bacteria that Grow Aerobically; Approved Standard-Sixth Edition. NCCLS Document M7-A6 and MIC Testing Supplemental Tables, M100-S13. NCCLS, Wayne, PA, USA.

CLINITEST® is a registered trademark of Miles, Inc.
CLINISTIX® is a registered trademark of Bayer Corporation.

SAGENT™

Mfd. for SAGENT Pharmaceuticals
Schaumburg, IL 60195
Made in USA
©2011 Sagent Pharmaceuticals, Inc.

May 2011

PACKAGE LABEL – PRINCIPAL DISPLAY PANEL

NDC 68258-8978-02 Rx only

CEFAZOLIN for Injection, USP

1 gram

Equivalent to 1 gram of cefazolin activity

For IM or IV Use